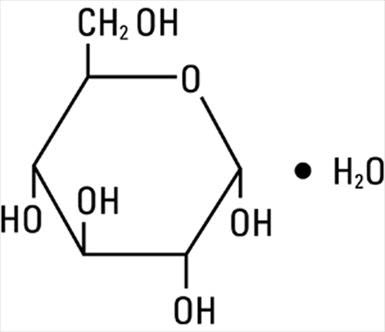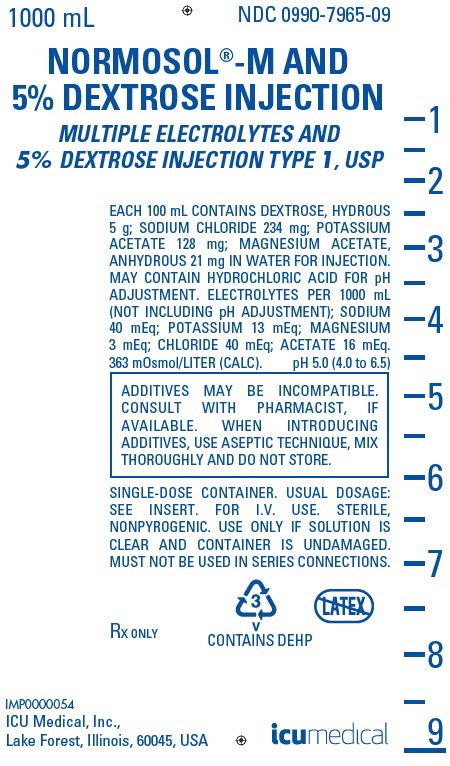 DRUG LABEL: NORMOSOL-M AND DEXTROSE
NDC: 0990-7965 | Form: INJECTION, SOLUTION
Manufacturer: ICU Medical Inc.
Category: prescription | Type: HUMAN PRESCRIPTION DRUG LABEL
Date: 20251024

ACTIVE INGREDIENTS: DEXTROSE MONOHYDRATE 5 g/100 mL; SODIUM CHLORIDE 234 mg/100 mL; POTASSIUM ACETATE 128 mg/100 mL; MAGNESIUM ACETATE 21 mg/100 mL
INACTIVE INGREDIENTS: WATER; HYDROCHLORIC ACID

NORMOSOL™-M and 5% DEXTROSE Injection
MULTIPLE ELECTROLYTES AND 5% DEXTROSE INJECTION TYPE 1, USP

Flexible Plastic Container

Rx Only

DESCRIPTION

Normosol-M and 5% Dextrose Injection (Multiple Electrolytes and 5% Dextrose Injection Type 1, USP) is a sterile, nonpyrogenic, hypertonic solution of balanced maintenance electrolytes and 5% dextrose injection in water for injection.

The solution is administered by intravenous infusion for parenteral maintenance of routine daily fluid and electrolyte requirements with minimal carbohydrate calories.

Each 100 mL contains dextrose, hydrous 5 g, sodium chloride, 234 mg, potassium acetate, 128 mg and magnesium acetate, anhydrous 21 mg. May contain hydrochloric acid for pH adjustment. The electrolyte content (not including hydrochloric acid) and other characteristics are as follows:

Sodium (Na^+) | 40 mEq/liter
Potassium (K^+) | 13 mEq/liter
Magnesium (Mg^++) | 3 mEq/liter
Chloride (Cl^−) | 40 mEq/liter
Bicarbonate (HCO3^−) as acetate | 16 mEq/liter
Caloric value (dextrose) | 170 Calories/liter
Tonicity | Hypertonic
Osmolarity | 363 mOsmol/liter (calc.)
pH (range) | 5.0 (4.0 to 6.5)

The solution contains no bacteriostat, antimicrobial agent or added buffer (except for pH adjustment) and is intended only for use as a single-dose injection. When smaller doses are required the unused portion should be discarded.

Normosol-M and 5% Dextrose Injection is a parenteral fluid, electrolyte and nutrient replenisher.

Dextrose, USP is chemically designated D-glucose monohydrate (C6H12O6 • H2O), a hexose sugar freely soluble in water. It has the following structural formula:

Sodium Chloride, USP is chemically designated NaCl, a white crystalline powder freely soluble in water.

Potassium Acetate, USP is chemically designated CH3COOK, colorless crystals or white crystalline powder very soluble in water.

Magnesium acetate is chemically designated Mg (C2H3O2)2, colorless or white crystals very soluble in water.

Water for Injection, USP is chemically designated H2O.

The flexible plastic container is fabricated from a specially formulated polyvinyl chloride. Water can permeate from inside the container into the overwrap but not in amounts sufficient to affect the solution significantly. Solutions in contact with the plastic container may leach out certain chemical components from the plastic in very small amounts; however, biological testing was supportive of the safety of the plastic container materials. Exposure to temperatures above 25°C/77°F during transport and storage will lead to minor losses in moisture content. Higher temperatures lead to greater losses. It is unlikely that these minor losses will lead to clinically significant changes within the expiration period.

CLINICAL PHARMACOLOGY

When administered intravenously, Normosol-M and 5% Dextrose Injection provides water and electrolytes (with dextrose as a readily available source of carbohydrate) for maintenance of daily fluid and electrolyte requirements, plus minimal carbohydrate calories. The electrolyte composition approaches that of the principal ions of normal plasma (extracellular fluid). The electrolyte concentration is hypotonic (112 mOsmol/liter) in relation to the extracellular fluid (280 mOsmol/liter). One liter provides approximately one-third of the average adult daily requirement for water and principal electrolytes in balanced proportions, with acetate as a bicarbonate alternate, plus 170 calories from dextrose.

Solutions containing carbohydrate in the form of dextrose restore blood glucose levels and supply calories. Carbohydrate in the form of dextrose may aid in minimizing liver glycogen depletion and exerts a protein-sparing action. Dextrose injected parenterally undergoes oxidation to carbon dioxide in water.

Sodium chloride in water dissociates to provide sodium (Na^+) and chloride (Cl^−) ions. Sodium (Na^+) is the principal cation of the extracellular fluid and plays a large part in the therapy of fluid and electrolyte disturbances. Chloride (Cl^−) has an integral role in buffering action when oxygen and carbon dioxide exchange occurs in the red blood cells. The distribution and excretion of sodium (Na^+) and chloride (Cl^−) are largely under the control of the kidney which maintains a balance between intake and output.

Potassium acetate in water dissociates to provide potassium (K^+) and acetate (CH3COO^−) ions. Potassium is the chief cation of body cells (160 mEq/liter of intracellular water). It is found in low concentration in plasma and extracellular fluids (3.5 to 5.0 mEq/liter) in a healthy adult and child over 10 days old; 3.5 to 6.0 mEq/liter in a child less than 10 days old. Potassium plays an important role in electrolyte balance. Normally about 80 to 90% of the potassium intake is excreted in the urine; the remainder in the stools and to a small extent, in the perspiration. The kidney does not conserve potassium well so that during fasting or in patients on a potassium-free diet, potassium loss from the body continues resulting in potassium depletion.

Magnesium acetate in water dissociates to provide magnesium (Mg^++) and acetate (CH3COO^−) ions. Magnesium is the second most plentiful cation of the intracellular fluids. It is an important cofactor for enzymatic reactions and plays an important role in neurochemical transmission and muscular excitability. Normal plasma concentration ranges from 1.5 to 2.5 or 3.0 mEq per liter. Magnesium is excreted solely by the kidney at a rate proportional to the plasma concentration and glomerular filtration.

Acetate anion (CH3COO^−), a source of hydrogen ion acceptors, serves as an alternate source of bicarbonate (HCO3^−) by metabolic conversion in the liver. This has been shown to proceed readily even in the presence of severe liver disease. Thus, acetate anion exerts a mild systemic antiacidotic action that may be advantageous during fluid and electrolyte replacement therapy.

Water is an essential constituent of all body tissues and accounts for approximately 70% of total body weight. Average normal adult daily requirement ranges from two to three liters (1.0 to 1.5 liters each for insensible water loss by perspiration and urine production). Average normal pediatric daily requirements are based on the child’s weight as described in the table below:

Weight | Fluid Requirements
Up to 10 kg | 100 mL/kg
11 to 20 kg | 1,000 mL + 50 mL/kg for each kg above 10 kg
Above 20 kg | 1,500 mL + 20 mL/kg for each kg above 20 kg

Water balance is maintained by various regulatory mechanisms. Water distribution depends primarily on the concentration of electrolytes in the body compartments and sodium (Na^+) plays a major role in maintaining physiologic equilibrium.

INDICATIONS AND USAGE

Normosol-M and 5% Dextrose Injection (Multiple Electrolytes and 5% Dextrose Injection Type 1, USP) is indicated for parenteral maintenance of routine daily fluid and electrolyte requirements with minimal carbohydrate calories from dextrose. Magnesium in the formula may help to prevent iatrogenic magnesium deficiency in patients receiving prolonged parenteral therapy.

CONTRAINDICATIONS

None known.

WARNINGS

Solutions containing sodium ions should be used with great care, if at all, in patients with congestive heart failure, severe renal insufficiency and in clinical states in which there exists edema with sodium retention.

Solutions which contain potassium should be used with great care, if at all, in patients with hyperkalemia, severe renal failure and in conditions in which potassium retention is present.

In patients with diminished renal function, administration of solutions containing sodium or potassium ions may result in sodium or potassium retention.

Solutions containing acetate should be used with great care in patients with metabolic or respiratory alkalosis, and in those conditions in which there is an increased level or an impaired utilization of acetate, such as severe hepatic insufficiency.

Administration of this solution can cause fluid and/or solute overloading resulting in dilution of serum electrolyte concentrations, overhydration, congested states or pulmonary edema. The risk of dilutional states is inversely proportional to the electrolyte concentrations of administered parenteral solutions. The risk of solute overload causing congested states with peripheral and pulmonary edema is directly proportional to the electrolyte concentrations of such solutions.

PRECAUTIONS

Clinical evaluation and periodic laboratory determinations are necessary to monitor changes in fluid balance, electrolyte concentrations, and acid-base balance during prolonged parenteral therapy or whenever the condition of the patient warrants such evaluation.

Caution must be exercised in the administration of parenteral fluids, especially those containing sodium ions, to patients receiving corticosteroids or corticotropin.

Solutions containing acetate should be used with caution, as excess administration may result in metabolic alkalosis.

Solutions containing dextrose should be used with caution in patients with known subclinical or overt diabetes mellitus.

Do not administer unless solution is clear and container is undamaged. Discard unused portion.

In very low birth weight infants, excessive or rapid administration of dextrose injection may result in increased serum osmolality and possible intracerebral hemorrhage.

Pregnancy Category C.

Animal reproduction studies have not been conducted with Normosol-M and 5% Dextrose Injection. It is also not known whether this solution can cause fetal harm when administered to a pregnant woman or can affect reproduction capacity. This solution should be given to a pregnant woman only if clearly needed.

Pediatric Use.

The safety and effectiveness in the pediatric population are based on the similarity of the clinical conditions of the pediatric and adult populations. In neonates and very small infants the volume of fluid may affect fluid and electrolyte balance.

Frequent monitoring of serum glucose concentrations is required when dextrose is prescribed to pediatric patients, particularly neonates and low birth weight infants.

ADVERSE REACTIONS

Reactions which may occur because of the solution or the technique of administration include febrile response, infection at the site of injection, venous thrombosis or phlebitis extending from the site of injection, extravasation and hypervolemia.

If an adverse reaction does occur, discontinue the infusion, evaluate the patient, institute appropriate therapeutic countermeasures and save the remainder of the fluid for examination if deemed necessary.

OVERDOSAGE

In the event of overhydration or solute overload, re-evaluate the patient and institute appropriate corrective measures. See WARNINGS, PRECAUTIONS and ADVERSE REACTIONS.

DOSAGE AND ADMINISTRATION

Normosol-M and 5% Dextrose Injection is administered by intravenous infusion. The dose is dependent upon the age, weight and clinical condition of the patient. A daily total amount of 1500 mL/M^2 of body surface will meet the usual adult daily requirements for water and principal electrolytes in patients unable to take anything by mouth. The usual daily maintenance amount for an average adult (70 kg and 1.8 square meters of body surface) is approximately three liters.

As reported in the literature, the dosage and constant infusion rate of intravenous dextrose must be selected with caution in pediatric patients, particularly neonates and low birth weight infants, because of the increased risk of hyperglycemia/hypoglycemia.

Drug Interactions

Additives may be incompatible. Consult with pharmacist, if available. When introducing additives, use aseptic technique, mix thoroughly and do not store.

To avoid precipitation of calcium salts that may occur when certain drugs are added, Normosol-M and 5% Dextrose Injection does not contain calcium.

Parenteral drug products should be inspected visually for particulate matter or discoloration prior to administration, whenever solution and container permit. See PRECAUTIONS.

INSTRUCTIONS FOR USE

To Open

Tear outer wrap at notch and remove solution container. Some opacity of the plastic due to moisture absorption during the sterilization process may be observed. This is normal and does not affect the solution quality or safety. The opacity will diminish gradually.

If supplemental medication is desired, follow directions below before preparing for administration.

To Add Medication

1. Prepare additive port.
2. Using aseptic technique and an additive delivery needle of appropriate length, puncture resealable additive port at target area, inner diaphragm and inject. Withdraw needle after injecting medication.
3. The additive port may be protected by covering with an additive cap.
4. Mix container contents thoroughly.

To Administer

1. Attach administration set per manufacturer’s instructions.
2. Regulate rate of administration per institutional policy.

WARNING: Do not use flexible container in series connections.

HOW SUPPLIED

Normosol-M and 5% Dextrose Injection (Multiple Electrolytes and 5% Dextrose Injection Type 1, USP) is supplied in single-dose flexible plastic containers.

NDC No. | Product | Container Size (mL)
0409-7965-03 | Normosol-M and 5% Dextrose Injection (Multiple Electrolytes and 5% Dextrose Inj., Type 1, USP) | 500
0990-7965-03 | Normosol-M and 5% Dextrose Injection (Multiple Electrolytes and 5% Dextrose Inj., Type 1, USP) | 500
0409-7965-09 | Normosol-M and 5% Dextrose Injection (Multiple Electrolytes and 5% Dextrose Inj., Type 1, USP) | 1000
0990-7965-09 | Normosol-M and 5% Dextrose Injection (Multiple Electrolytes and 5% Dextrose Inj., Type 1, USP) | 1000

ICU Medical is transitioning NDC codes from the "0409" to a "0990" labeler code. Both NDC codes are expected to be in the market for a period of time.

Store at 20 to 25°C (68 to 77°F). [See USP Controlled Room Temperature.]

Revised: March, 2020

IFU0000171

ICU Medical, Inc., Lake Forest, Illinois, 60045, USA

PRINCIPAL DISPLAY PANEL - 1000 mL Bag Label

1000 mL
NDC 0990-7965-09

NORMOSOL®-M AND
5% DEXTROSE INJECTION

MULTIPLE ELECTROLYTES AND
5% DEXTROSE INJECTION TYPE 1, USP

EACH 100 mL CONTAINS DEXTROSE, HYDROUS
5 g; SODIUM CHLORIDE 234 mg; POTASSIUM
ACETATE 128 mg; MAGNESIUM ACETATE,
ANHYDROUS 21 mg IN WATER FOR INJECTION.
MAY CONTAIN HYDROCHLORIC ACID FOR pH
ADJUSTMENT. ELECTROLYTES PER 1000 mL
(NOT INCLUDING pH ADJUSTMENT); SODIUM
40 mEq; POTASSIUM 13 mEq; MAGNESIUM
3 mEq; CHLORIDE 40 mEq; ACETATE 16 mEq.
363 mOsmol/LITER (CALC).
pH 5.0 (4.0 to 6.5)

ADDITIVES MAY BE INCOMPATIBLE.
CONSULT WITH PHARMACIST, IF
AVAILABLE. WHEN INTRODUCING
ADDITIVES, USE ASEPTIC TECHNIQUE, MIX
THOROUGHLY AND DO NOT STORE.

SINGLE-DOSE CONTAINER. USUAL DOSAGE:
SEE INSERT. FOR I.V. USE. STERILE,
NONPYROGENIC. USE ONLY IF SOLUTION IS
CLEAR AND CONTAINER IS UNDAMAGED.
MUST NOT BE USED IN SERIES CONNECTIONS.

RX ONLY

3
V
CONTAINS DEHP

IMP0000054
ICU Medical, Inc.,
Lake Forest, Illinois, 60045, USA

icumedical